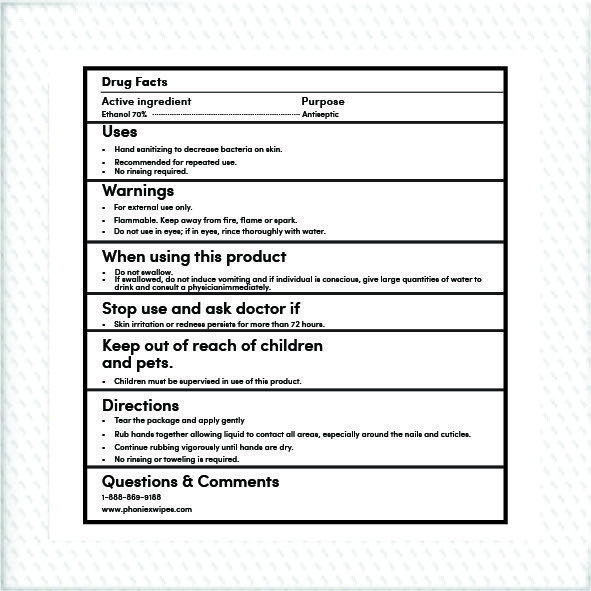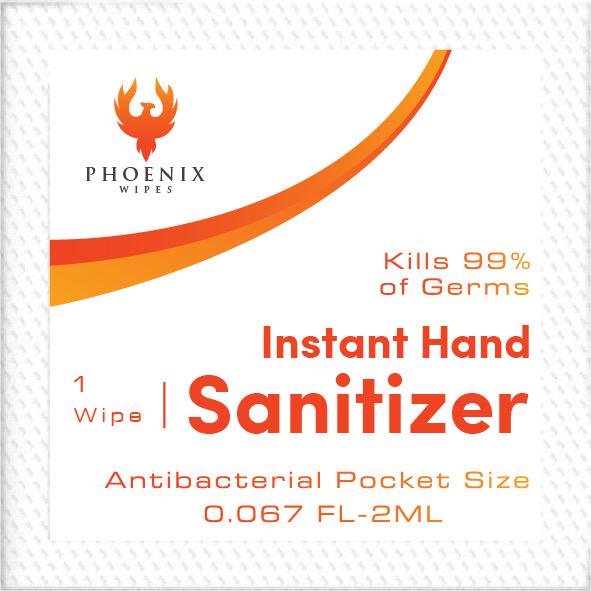 DRUG LABEL: Hand Sanitizer
NDC: 78837-202 | Form: GEL
Manufacturer: Phoenix Wipes Inc
Category: otc | Type: HUMAN OTC DRUG LABEL
Date: 20200608

ACTIVE INGREDIENTS: ALCOHOL 70 mL/70 mL
INACTIVE INGREDIENTS: WATER; 1-(3,4-DIMETHOXYPHENYL)PROPANE-1,2-DIOL

Active Ingredient

70 % Alcohol vv Purpose: Antiseptic

PACKAGE LABEL

2ml NDC 78837-202-20